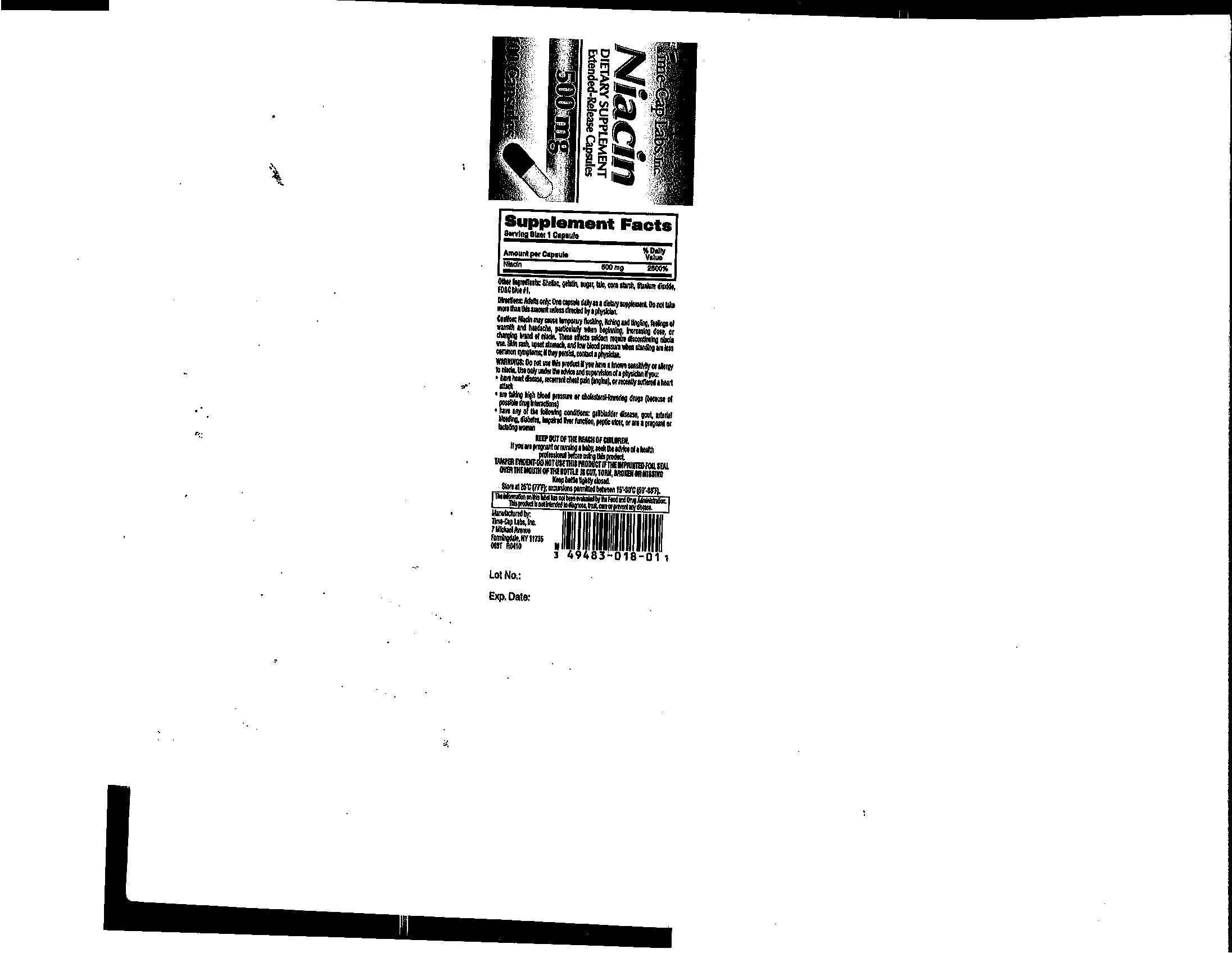 DRUG LABEL: NIACIN
NDC: 49483-018 | Form: CAPSULE, EXTENDED RELEASE
Manufacturer: TIME CAP LABS INC
Category: other | Type: DIETARY SUPPLEMENT
Date: 20140404

ACTIVE INGREDIENTS: NIACIN 500 mg/1 1
INACTIVE INGREDIENTS: SHELLAC; GELATIN; SUCROSE; TALC; TITANIUM DIOXIDE; FD&C BLUE NO. 1

STATEMENT OF IDENTITY

Niacin Dietary Supplement Extended Release Capsules 500 mg

Do not use this product if you have a known sensitivity or allergy to niacin. Use only under the advice and supervision of a physician if you:have heart disease, abnormal chest pain (angina)or recently suffered a heart attack; are taking high blood pressure or cholestrol lowering drugs(because of possible drug interactions); have any of the following conditions: gallbladder disease, gout, arterial bleeding, diabetes, imparied liver function, peptic ulcer, or are a pregnant or lactating woman.

Keep out of Reach of children. If you are pregnant or nursing a baby, seek the advice of a health professinoal before using this product

HEALTH CLAIM

DIETARY SUPPLEMENT